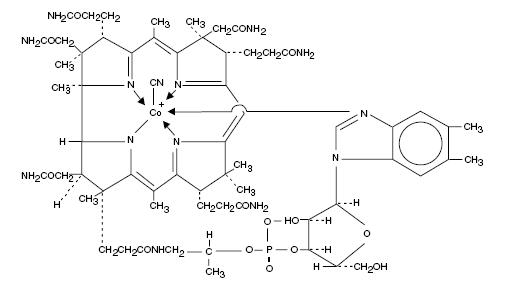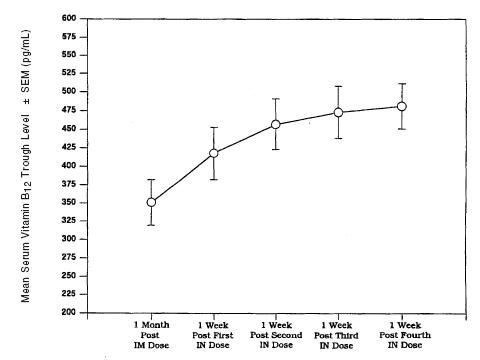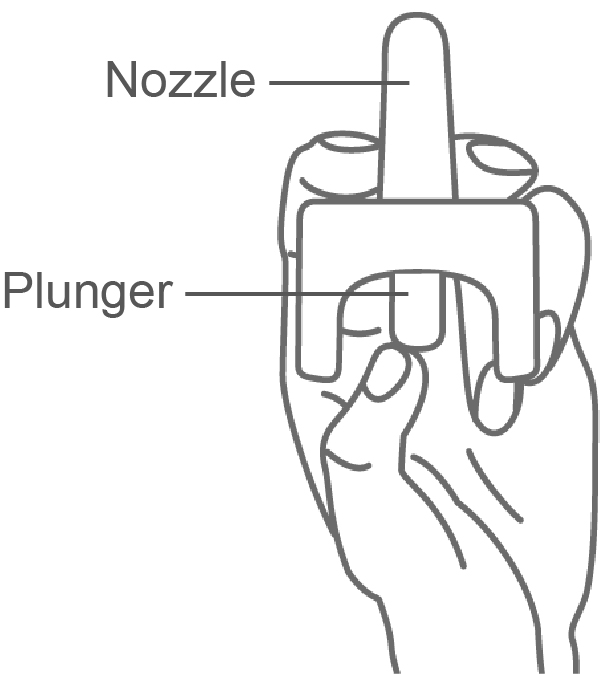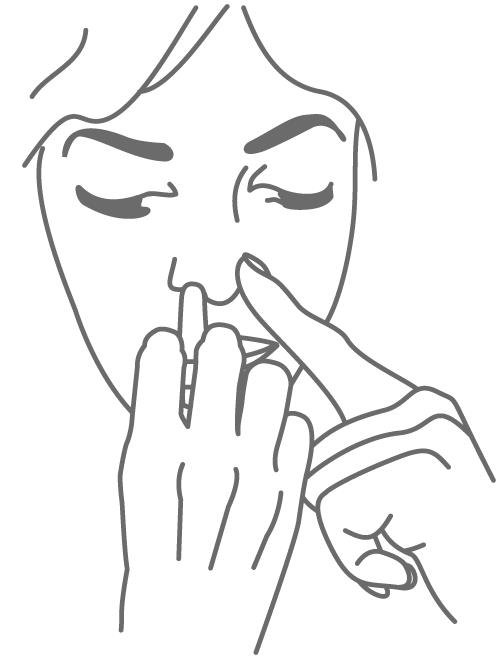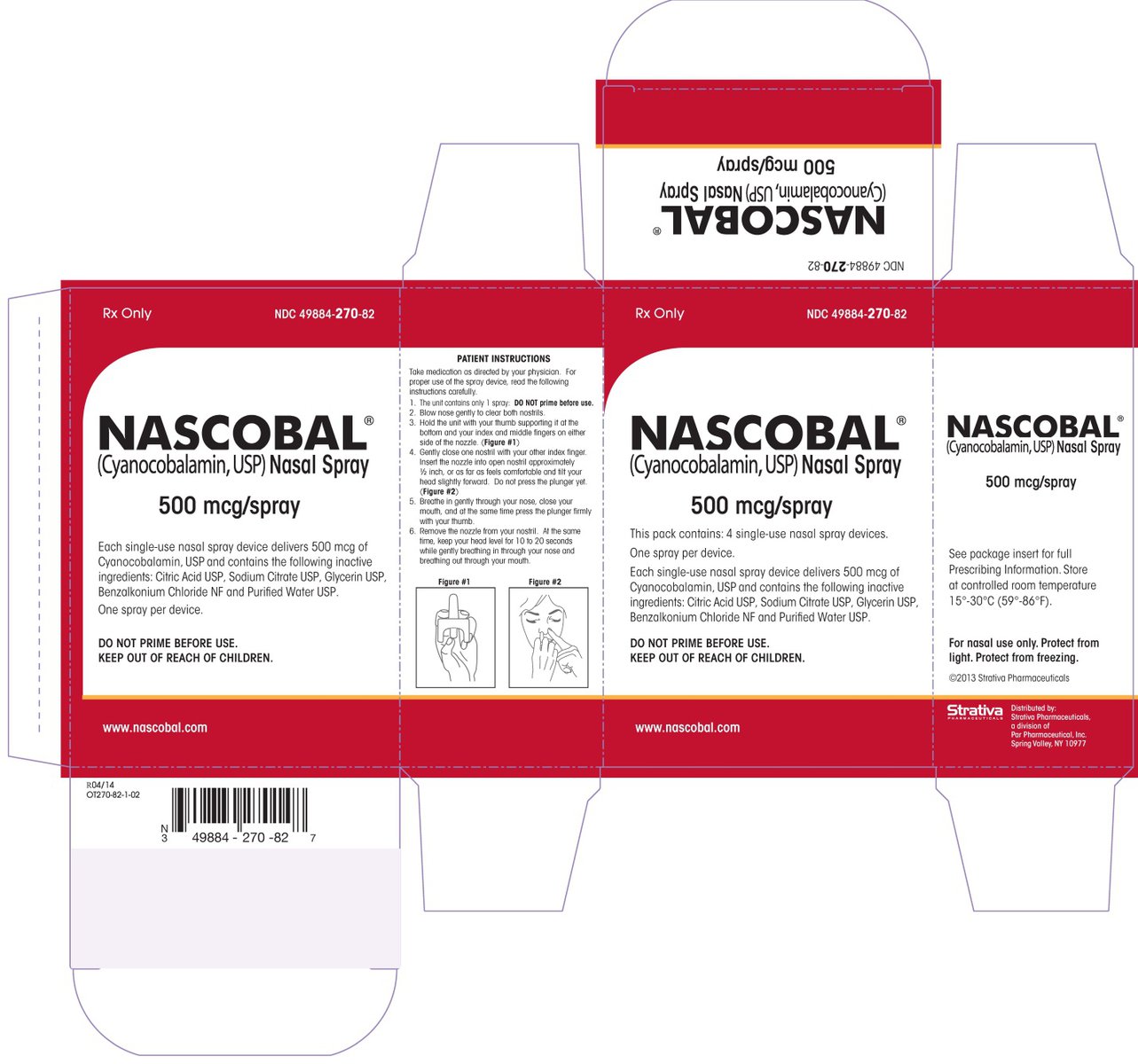 DRUG LABEL: Nascobal
NDC: 49884-270 | Form: SPRAY
Manufacturer: ENDO USA, Inc.
Category: prescription | Type: HUMAN PRESCRIPTION DRUG LABEL
Date: 20181130

ACTIVE INGREDIENTS: CYANOCOBALAMIN 500 ug/1 1
INACTIVE INGREDIENTS: SODIUM CITRATE; CITRIC ACID MONOHYDRATE; GLYCERIN; BENZALKONIUM CHLORIDE

HIGHLIGHTS OF PRESCRIBING INFORMATION

These highlights do not include all the information needed to use NASCOBAL® NASAL SPRAY safely and effectively. See full prescribing information for NASCOBAL® NASAL SPRAY.
NASCOBAL (cyanocobalamin nasal spray)
Initial U.S. Approval: 1942

1 INDICATIONS AND USAGE

NASCOBAL is a vitamin B12 indicated for:

- Vitamin B12 maintenance therapy in adult patients with pernicious anemia who are in remission following intramuscular vitamin B12 therapy and who have no nervous system involvement(1)
- Treatment of adult patients with dietary, drug-induced, or malabsorption-related vitamin B12 deficiency not due to pernicious anemia (1)
- Prevention of vitamin B12 deficiency in adult patients with vitamin B12 requirements in excess of normal (1)

Limitations of Use:

- Should not be used for the vitamin B12 absorption test (Schilling test). (1)
- In patients with correctible or temporary causes of vitamin B12 deficiency the benefit of continued long-term use following correction of vitamin B12 deficiency and underlying disease has not been established. (1)
- In patients with active symptoms of nasal congestion, allergic rhinitis or upper respiratory infection effectiveness has not been established. (1)

2 DOSAGE AND ADMINISTRATION

- Prior to treatment, obtain hematocrit, reticulocyte count, vitamin B12, folate, and iron levels. (2.1)
- The recommended initial dose is one spray (500 mcg) in one nostril once weekly.(2.2)
- Administer at least one hour before or one hour after ingestion of hot foods or liquids. (2.2)
- Monitor serum B12 levels periodically.Obtain a serum B12 level and peripheral blood count one month after treatment initiation, then subsequently at intervals of 3 to 6 months. (2.3)
- If serum levels of B12 decline after one month of treatment, consider increasing the dose. Assess serum B12 level one month after each dose adjustment.If serum B12 levels are persistently low, consider alternative therapy (e.g., intramuscular or subcutaneous vitamin B12 therapy). (2.3)
- See Full Prescibing Information to see what other therapies should be administered with NASCOBAL. (2.4)

3 DOSAGE FORMS AND STRENGTHS

Nasal spray: 500 mcg cyanocobalamin/0.1 mL (per actuation) (3)

4 CONTRAINDICATIONS

• Hypersensitivity to cobalt, vitamin B12 or any excipients (4)

5 WARNINGS AND PRECAUTIONS

• Severe Optic Atrophy in Patients with Leber’s Disease:Patients with early Leber’s disease who were treated with vitamin B12 suffered severe and swift optic atrophy. NASCOBAL is not recommended for use in these patients.(5.1)

• Anaphylactic Reactions: Anaphylactic shock and death have been reported after parenteral vitamin B12 administration. If patients are to start NASCOBAL before having tolerated cyanocobalamin parenterally, consider administering an intradermal test dose of parenteral vitamin B12 to patients suspected of cyanocobalamin hypersensitivity. (2.1,5.2)

• Masking of Folate Deficiency with Vitamin B12 Use: Doses of vitamin B12 exceeding 10 mcg daily may produce hematologic response in patients with folate deficient megaloblastic anemia and may therefore mask a previously unrecognized folate deficiency. Assess both vitamin B12 and folate levels prior to initiating therapy with NASCOBAL or with folic acid. (5.3)

• Hypokalemia and Thrombocytosis Due to Intense Treatment of Megaloblastic Anemia: Hypokalemia and sudden death may occur in severe megaloblastic anemia that is treated intensely with vitamin B12. Monitor serum potassium levels and platelet count during therapy. (5.4)

• Unmasking of Polycythemia Vera:Vitamin B12 deficiency may suppress the signs of polycythemia vera. Treatment with NASCOBAL may unmask this condition. Patients exhibiting clinical or hematologic response consistent with polycythemia vera should be referred for further evaluation. (5.5)

6 ADVERSE REACTIONS

The most common adverse reactions (≥ 4%) were infection, headache, glossitis, paresthesia, asthenia, nausea and rhinitis (6.1)

To report SUSPECTED ADVERSE REACTIONS, contact Par Pharmaceutical, Inc. at 1-800-828-9393 or FDA at 1-800-FDA-1088 or www.fda.gov/medwatch.

See 17 for PATIENT COUNSELING INFORMATION and FDA-approved patient labeling

8 USE IN SPECIFIC POPULATIONS

See Patient Counseling Information.

FULL PRESCRIBING INFORMATION

1 INDICATIONS AND USAGE

NASCOBAL is indicated for:

- Vitamin B12 maintenance therapy in adult patients with pernicious anemia who are in remission following intramuscular vitamin B12 therapy and who have no nervous system involvement
- Treatment of adult patients with dietary, drug-induced, or malabsorption-related vitamin B12 deficiency not due to pernicious anemia
- Prevention of vitamin B12 deficiency in adult patients with vitamin B12 requirements in excess of normal
  Limitations of Use
- NASCOBAL should not be used for the vitamin B12 absorption test (Schilling test).
- In patients with correctible or temporary causes of vitamin B12 deficiency, the benefit of continued long-term use of NASCOBAL following adequate correction of vitamin B12 deficiency and underlying disease has not been established.
- The effectiveness of NASCOBAL in patients with active symptoms of nasal congestion, allergic rhinitis or upper respiratory infection has not been determined. Treatment with NASCOBAL should be deferred until symptoms have subsided.

2 DOSAGE AND ADMINISTRATION

2.1 Testing and Other Considerations Prior to Dosing

Prior to treatment, obtain hematocrit, reticulocyte count, vitamin B12, folate, and iron levels [see Dosage and Administration (2.4)]. Consider the potential for concomitant drugs to interfere with vitamin B12 and folate diagnostic blood assays [see Drug Interactions (7)].

In patients with suspected cobalamin hypersensitivity, consider administering an intradermal test dose of parenteral vitamin B12 prior to use of NASCOBAL [see Warnings and Precautions (5.2)].

2.2 Recommended Dosage

The recommended initial dose of NASCOBAL is one spray (500 mcg) administered in ONE nostril once weekly. Administer NASCOBAL at least one hour before or one hour after ingestion of hot foods or liquids since hot foods may cause nasal secretions and a resulting loss of medication. Defer use of NASCOBAL in patients with nasal congestion, allergic rhinitis, or upper respiratory infections until after symptoms have subsided.

2.3 Monitoring, Dosage Modifications, and Treatment Duration

Monitoring for Response and Safety

Monitor serum B12 levels periodically during therapy to establish adequacy of therapy. Obtain a serum B12 level and peripheral blood count one month after treatment initiation, then subsequently at intervals of 3 to 6 months [see Warnings and Precautions (5.3)].

Dosage Modifications

If serum levels of B12 decline after one month of treatment with NASCOBAL, consider increasing the dose. Assess serum B12 level one month after each dose adjustment. If serum B12 levels are persistently low, consider alternative therapy (e.g., intramuscular or subcutaneous vitamin B12 therapy).

Treatment Duration

In patients whose underlying cause of vitamin B12 deficiency has been corrected and are deemed no longer at risk for vitamin B12 deficiency, discontinue NASCOBAL. The safety and effectiveness of continued long-term use in these individuals has not been established.

In patients with pernicious anemia, continue appropriate vitamin B12 treatment indefinitely.

2.4 Administration of NASCOBAL with Other Therapy

NASCOBAL should be administered with other therapy(ies) in:

- Patients with concurrent folate and vitamin B12 deficiency:Administer folic acid in addition to NASCOBAL
- Patients with concurrent iron and vitamin B12 deficiency:Administer iron in addition to NASCOBAL
- Patients with correctible causes of vitamin B12 deficiency:Consider measures to treat the underlying condition associated with vitamin B12 deficiency in addition to treatment with NASCOBAL

3 DOSAGE FORMS AND STRENGTHS

Nasal spray: 500 mcg/0.1 mL (per actuation), packaged in a single-use device containing 0.125 mL of solution

4 CONTRAINDICATIONS

NASCOBAL is contraindicated in patients with hypersensitivity to cobalt and/or vitamin B12 or any of its excipients [see Warnings and Precautions (5.2)]. Anaphylactic shock and death have been reported after parenteral vitamin B12 administration in sensitive patients.

5 WARNINGS AND PRECAUTIONS

5.1 Severe Optic Atrophy in Patients with Leber’s Disease

Patients with early Leber’s disease (hereditary optic nerve atrophy) who were treated with vitamin B12 suffered severe and swift optic atrophy. Cyanocobalamin products, including NASCOBAL, is not recommended for use in patients with Leber’s optic atrophy. For patients with Leber’s disease requiring vitamin B12, consider alternative therapy (e.g., hydroxocobalamin) for B12 supplementation.

5.2 Anaphylactic Reactions

Anaphylactic shock and death have been reported after parenteral vitamin B12 administration. If patients are to start NASCOBAL before having tolerated cyanocobalamin parenterally, consider administering an intradermal test dose of parenteral vitamin B12 to patients suspected of cyanocobalamin hypersensitivity [see Dosage and Administration (2.1)].

5.3 Masking of Folate Deficiency with Vitamin B12 Use

Doses of vitamin B12 exceeding 10 mcg daily may produce hematologic response in patients with folate deficient megaloblastic anemia and may therefore mask a previously unrecognized folate deficiency. Vitamin B12 is not a substitute for folic acid [see Dosage and Administration (2.4)]. Assess both vitamin B12 and folate levels prior to initiating therapy with vitamin B12, including NASCOBAL, or with folic acid [see Dosage and Administration (2.1)].

5.4 Hypokalemia and Thrombocytosis Due to Intense Treatment of Megaloblastic Anemia

Hypokalemia and sudden death may occur in severe megaloblastic anemia that is treated intensely with vitamin B12. Hypokalemia and thrombocytosis can occur upon conversion of severe megaloblastic anemia to normal erythropoiesis with vitamin B12 therapy. Therefore, serum potassium levels and platelet count should be monitored carefully during therapy [see Dosage and Administration (2.3)].

5.5 Unmasking of Polycythemia Vera

Vitamin B12 deficiency may suppress the signs of polycythemia vera. Treatment with vitamin B12 may unmask this condition. Patients exhibiting clinical or hematologic response consistent with polycythemia vera should be referred for further evaluation.

6 ADVERSE REACTIONS

The following serious adverse reactions are described elsewhere in the labeling:

- Severe Optic Atrophy in Patients with Leber’s Disease [see Warnings and Precautions (5.1)].
- Anaphylactic Reactions [see Warnings and Precautions (5.2)].
- Hypokalemia and Thrombocytosis Due to Intense Treatment of Megaloblastic Anemia [see Warnings and Precautions (5.4)].

6.1 Clinical Trials Experience

Because clinical trials are conducted under widely varying conditions, adverse reaction rates observed in the clinical trials of a drug cannot be directly compared to rates in the clinical trials of another drug and may not reflect the rates observed in practice. The adverse reactions described in Table 1 below are based on data from an eight week cross over trial in which vitamin B12 deficient patients in hematologic remission received one vitamin B12 intramuscular injection (N=25) and then received once weekly intranasal administration of another nasal cyanocobalamin formulation (N=24) for 4 weeks.

Table 1. Adverse Reactions Following Intranasal or Intramuscular Administration of Cyanocobalamin In Vitamin B12 Deficient Patients in Hematologic Remission
Adverse Reaction | Number of Patients (%)
Adverse Reaction | Another Cyanocobalamin Nasal Formulation, 500 mcg (n=24) | Intramuscular Cyanocobalamin*, 100 mcg (n=25)
Infection a | 3 (13) | 3 (12)
Headache | 1 (4) | 5 (20)
Asthenia | 1 (4) | 4 (16)
Nausea | 1 (4) | 1 (4)
Glossitis | 1 (4) | 0 (0)
Paresthesia | 1 (4) | 1 (4)
Rhinitis | 1 (4) | 2 (8)
a Sore throat, common cold
* The data are not an adequate basis for comparison of rates between the study drug and the active control

7 DRUG INTERACTIONS

Chloramphenicol may decrease the efficacy of NASCOBAL when used for treatment of anemia. If NASCOBAL is used for the treatment of anemia concomitantly with chloramphenicol, monitor for reduced efficacy and if needed, consider an alternative therapy

8 USE IN SPECIFIC POPULATIONS

8.1 Pregnancy

Risk Summary

The limited available data on NASCOBAL in pregnant women are insufficient to inform a drug-associated risk of adverse developmental outcomes. However, vitamin B12 is an essential vitamin and requirements are increased during pregnancy.

Animal reproduction studies have not been conducted with vitamin B12.

The estimated background risk of major birth defects and miscarriage for the indicated population is unknown. In the U.S. general population, the estimated background risks of major birth defects and miscarriage in clinically recognized pregnancies is 2-4% and 15-20%, respectively.

8.2 Lactation

Risk Summary

Vitamin B12 is present in the milk of lactating women in concentrations which approximate the mother’s vitamin B12 blood level. Vitamin B12 does not appear to pose more than a minimal risk to breastfeeding children.

8.4 Pediatric Use

Safety and effectiveness have not been established in pediatric patients.

8.5 Geriatric Use

Clinical studies of NASCOBAL did not include sufficient numbers of subjects aged 65 and over to determine whether they respond differently from younger subjects. Other reported clinical experience has not identified differences in responses between the elderly and younger patients.

11 DESCRIPTION

Cyanocobalamin is a synthetic form of vitamin B12. The chemical name is 5,6-dimethyl-benzimidazolyl cyanocobamide. The cobalt content is 4.35%. The molecular formula is C63H88CoN14O14P, which corresponds to a molecular weight of 1355.38 and the following structural formula:

Figure 1. Nascobal Chemical Structure

Cyanocobalamin occurs as dark red crystals or orthorhombic needles or crystalline red powder. It is very hygroscopic in the anhydrous form, and sparingly to moderately soluble in water (1:80). Its pharmacologic activity is destroyed by heavy metals (iron) and strong oxidizing or reducing agents (vitamin C), but not by autoclaving for short periods of time (15-20 minutes) at 121°C. The vitamin B12 coenzymes are very unstable in light.

NASCOBAL (cyanocobalamin) nasal spray is a solution of cyanocobalamin, USP (vitamin B12) for administration as a spray to the nasal mucosa. Each single-use device of NASCOBAL NASAL SPRAY contains 0.125 mL of a 500 mcg/0.1 mL solution of cyanocobalamin with, benzalkonium chloride in purified water, citric acid, glycerin and sodium citrate. The spray solution has a pH between 4.5 and 5.5. Each spray delivers an average of 500 mcg of cyanocobalamin per actuation.

12 CLINICAL PHARMACOLOGY

12.1 Mechanism of Action

Vitamin B12 can be converted to coenzyme B12 in tissues, and as such is essential for conversion of methylmalonate to succinate and synthesis of methionine from homocysteine, a reaction which also requires folate. In the absence of coenzyme B12, tetrahydrofolate cannot be regenerated from its inactive storage form, 5-methyltetrahydrofolate, and a functional folate deficiency occurs. Vitamin B12 also may be involved in maintaining sulfhydryl (SH) groups in the reduced form required by many SH-activated enzyme systems. Through these reactions, vitamin B12 is associated with fat and carbohydrate metabolism and protein synthesis.

12.2 Pharmacodynamics

Parenteral (intramuscular) administration of vitamin B12 completely reverses the megaloblastic anemia and GI symptoms of vitamin B12 deficiency; the degree of improvement in neurologic symptoms depends on the duration and severity of the lesions, although progression of the lesions is immediately arrested. In pernicious anemia patients, once weekly intranasal dosing with 500 mcg B12 gel resulted in a consistent increase in pre-dose serum B12 levels during one month of treatment (p < 0.003) above that seen one month after 100 mcg intramuscular dose (Figure 2).

Figure 2. Vitamin B12 Serum Trough Levels After Intramuscular Solution (IM) of 100 mcg and Nasal Gel (IN) Administration of 500 mcg Cyanocobalamin After Weekly Doses.

12.3 Pharmacokinetics

Absorption

Vitamin B12 is bound to intrinsic factor during transit through the stomach; separation occurs in the terminal ileum in the presence of calcium, and vitamin B12 enters the mucosal cell for absorption. It is then transported by the transcobalamin binding proteins. A small amount (approximately 1% of the total amount ingested) is absorbed by simple diffusion, but this mechanism is adequate only with very large doses.

A three way crossover study in 25 fasting healthy subjects was conducted to compare the bioavailability of the B12 nasal spray to the B12 nasal gel and to evaluate the relative bioavailability of the nasal formulations as compared to the intramuscular injection. The peak concentrations after administration of intranasal spray were reached in 1.25 +/- 1.9 hours. The mean peak plasma concentration (Cmax) of B12, obtained after baseline correction, following administration of intranasal spray were 748 +/-549 pg/mL. The bioavailability of the B12 nasal spray was found to be 10% less than the B12 nasal gel.

Distribution

In the blood, B12 is bound to transcobalamin II, a specific B-globulin carrier protein, and is distributed and stored primarily in the liver and bone marrow.

Elimination

About 3-8 mcg of B12 is secreted into the GI tract daily via the bile and undergoes some enterohepatic recycling; in normal subjects with sufficient intrinsic factor, all but about 1 mcg is reabsorbed. When B12 is administered in doses which saturate the binding capacity of plasma proteins and the liver, the unbound B12 is rapidly eliminated in the urine. Retention of B12 in the body is dose-dependent. About 80-90% of an intramuscular dose up to 50 mcg is retained in the body; this percentage drops to 55% for a 100 mcg dose, and decreases to 15% when a 1000 mcg dose is given.

13 NONCLINICAL TOXICOLOGY

13.1 Carcinogenesis and Mutagenesis and Impairment of Fertility

Long-term studies in animals to evaluate carcinogenic potential have not been done.

16 HOW SUPPLIED/STORAGE AND HANDLING

NASCOBAL is a nasal spray available in a dosage strength of 500 mcg cyanocobalamin/0.1 mL (per actuation). It is supplied in boxes of 4 single-use nasal spray devices and a package insert (NDC 49884-270-82).

Protect from light. Keep covered in carton until ready to use. Store upright at controlled room temperature 15°C to 30°C (59°F to 86°F). Protect from freezing.

17 PATIENT COUNSELING INFORMATION

Advise the patient to read the FDA-approved patient labeling (Instructions for Use).

Importance of Adherence to Therapy and Follow-up

Advise patients of the importance of adhering to therapy to prevent the development, recurrence, or progression of anemia and the development or progression of neurological manifestations.

Patients experiencing symptomatic nasal congestion, allergic rhinitis or an upper respiratory infection should be advised to defer treatment with NASCOBAL until symptoms have subsided.

Counsel patients on the importance of returning for follow-up blood tests every 3 to 6 months to confirm adequacy of therapy [see Dosage and Administration (2.3)].

Specific Instructions for Administration

Advise patients to administer NASCOBAL at least one hour before or one hour after ingestion of hot foods or liquids since hot foods may cause nasal secretions and a resulting loss of medication.

Use of Nasal Spray Device

Provide patients with instructions on nasal administration of NASCOBAL. In addition to alerting patients to the instructions contained in the Instructions For Use and instructions supplied on each carton, demonstrate procedures for use to each patient.

PATIENT INFORMATION

NASCOBAL (NAZ. co. bal)

(cyanocobalamin) nasal spray

NASCOBAL is for use in your nose only.

What is NASCOBAL?

NASCOBAL is a prescription medicine used:

- for maintenance therapy to treat vitamin B12 deficiency (low levels of vitamin B12) in adults with pernicious anemia who achieved healthy vitamin B12 levels after receiving vitamin B12 shots and do not have nervous system problems.
- to treat vitamin B12 deficiency caused by:
  - certain food limitations,
  - oother medicines that cause vitamin B12 deficiency, or
  - lack of absorption (malabsorption) that are not related to pernicious anemia.
- to prevent vitamin B12 deficiency in adults who require higher amounts of vitamin B12.

NASCOBAL should not be used for a vitamin B12 absorption test known as the Schilling test.

In people that have corrected or have fixed their short-term causes of vitamin B12 deficiency, the benefit of continued long-term use of NASCOBAL is not known after vitamin B12 deficiency has been corrected.

It is not known if NASCOBAL is effective in people that currently have a stuffy nose, allergies or an upper respiratory infection. You should wait until these symptoms have gone away before using NASCOBAL.

It is not known if NASCOBAL is safe and effective in children.

Do not use NASCOBAL if you are allergic to cobalt, vitamin B12, cyanocobalamin or any ingredients in NASCOBAL. See the end of this leaflet for a complete list of ingredients in NASCOBAL.

Before you use NASCOBAL, tell your healthcare provider about all of your medical conditions, including if you:

- have a history of a certain disease that effects or weakens the optic nerve in your eye (early Leber’s disease). NASCOBAL is not recommended in people with Leber’s optic atrophy.
- have had an allergic reaction to vitamin B12 injections or intravenous (IV) infusion.
- have low levels of folate or iron.
- are pregnant or plan to become pregnant. It is not known if NASCOBAL will harm your unborn baby.

Tell your healthcare provider about all the medicines you take, including prescription and over-the-counter medicines, vitamins, and herbal supplements.

How should I use NASCOBAL?

- See the Instructions for Use at the end of this leaflet for instructions on how to use NASCOBAL.
- You should use NASCOBAL exactly as your healthcare provider tells you to use it.
- Your healthcare provider will tell you how much NASCOBAL to use and when to use it.
- You should not use NASCOBAL 1 hour before or 1 hour after eating hot foods or drinking hot liquids. Eating hot food or drinking hot liquids too soon before or after taking NASCOBAL can cause you to have a runny nose and can affect the amount of NASCOBAL you receive.
- Your healthcare provider may do certain blood tests before you use NASCOBAL and every 3 to 6 months while you are taking it.
- Your healthcare provider may change your dose based on the results of your blood tests.

What are the possible side effects of NASCOBAL?

NASCOBAL can cause serious side effects, including:

- Weaken your eye nerve in patients with early Leber’s disease. Tell your healthcare provider if you or your family has a history of early Leber’s disease.
- Serious allergic reactions. Serious life-threatening allergic reactions including death have happened in people who have received vitamin B12 by injection or by intravenous (IV) infusion (parenteral). Tell your healthcare provider if you have ever had a reaction after you received vitamin B12 by injection or IV infusion.
- Hiding (masking) a folate deficiency. Your healthcare provider may do certain blood tests to check your vitamin B12 and folate levels.
- Low potassium levels (hypokalemia) and low blood platelets (thrombocytopenia) can happen in people with serious megaloblastic anemia. Your healthcare provider may monitor your potassium levels and platelets counts during your treatment with NASCOBAL.

The most common side effects of NASCOBAL include:

- infection
- headache
- feeling weak
- nausea
- swelling of your tongue
- runny nose
- tingling of the hands and feet

These are not all of the possible side effects of NASCOBAL.

Call your doctor for medical advice about side effects. You may report side effects to FDA at 1-800-FDA-1088.

General information about the safe and effective use of NASCOBAL.

Medicines are sometimes prescribed for purposes other than those listed in a Patient Information leaflet. Do not use NASCOBAL for a condition for which it was not prescribed. Do not give NASCOBAL to other people, even if they have the same symptoms that you have. It may harm them. You can ask your pharmacist or healthcare provider for information about NASCOBAL that is written for health professionals.

What are the ingredients in NASCOBAL?

Active ingredient: cyanocobalamin

Inactive ingredients: benzalkonium chloride in purified water, citric acid, glycerin and sodium citrate.

Manufactured by:

Par Pharmaceuticals, Inc.

1 Ram Ridge Road

Chestnut Ridge, NY 10977

For more information, go to www.parpharm.com or call 1-800-828-9393.

This Patient Information has been approved by the U.S. Food and Drug Administration.

Revised: 11/2018

INSTRUCTIONS FOR USE

NASCOBAL (NAZ. co. bal)

(cyanocobalamin) nasal spray

NASCOBAL is for use in your nose only.

Read this Instructions for Use before you start using NASCOBAL (cyanocobalamin) nasal spray and each time you get a refill. There may be new information. This information does not take the place of talking to your healthcare provider about your medical condition or your treatment.

Your healthcare provider should teach you how to use NASCOBAL before you use it for the first time. If you have any questions or do not understand the instructions, talk with your healthcare provider or pharmacist.

NASCOBAL spray contains only 1 spray. You do not need to prime NASCOBAL before you use it.

If you are eating hot foods or liquids, use NASCOBAL at least one hour before or one hour afterwards because eating hot food or drinking hot liquids too soon before or after taking NASCOBAL can cause you to have a runny nose and can affect the amount of NASCOBAL you receive.

How to use NASCOBAL?

Step 1. Blow your nose gently to clear both nostrils.

Step 2. Hold NASCOBAL with your thumb on the bottom and your index (pointer) finger and middle finger on either side of the nozzle (see Figure A).

(Figure A)

Step 3. Gently close 1 side of your nose (nostril) with your other index finger. Insert the nozzle into the open nostril about half an inch or as far as it feels comfortable and tilt your head slightly forward (see Figure B). Do not press the plunger yet.

(Figure B)

Step 4. Breathe in gently through your nose, close your mouth, and at the same time press the plunger firmly upwards with your thumb.

Step 5. Remove the nozzle from your nostril. At the same time, keep your head straight for 10 to 20 seconds while gently breathing in through your nose and breathing out through your mouth.

How to dispose of (throw away) NASCOBAL?

NASCOBAL can be disposed of in your household trash. Place the NASCOBAL nasal spray in a container such as a zip-top or sealable plastic bag, and throw the container away in your household trash.

This Instructions for Use has been approved by the U.S. Food and Drug Administration.

Revised: 11/2018

PACKAGE LABEL

image-6